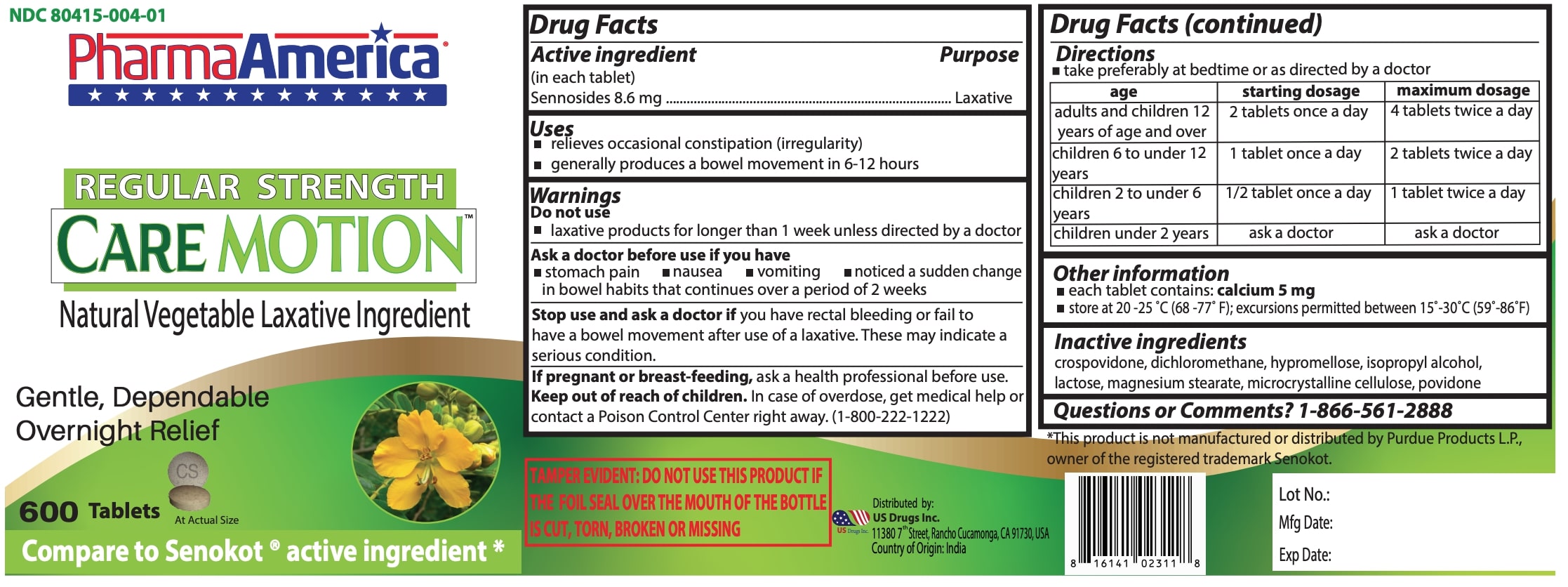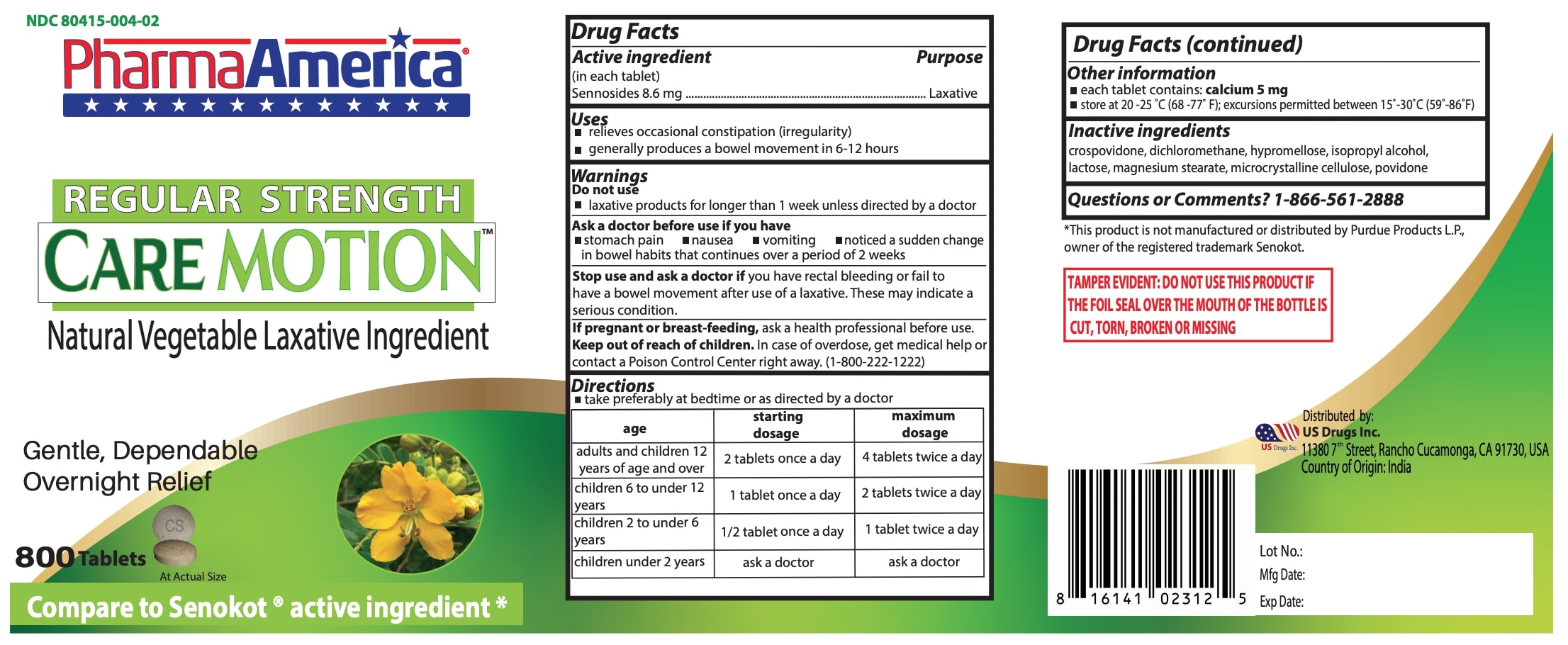 DRUG LABEL: CAREMOTION
NDC: 80415-004 | Form: TABLET
Manufacturer: US Drugs Inc.
Category: otc | Type: HUMAN OTC DRUG LABEL
Date: 20211118

ACTIVE INGREDIENTS: SENNOSIDES 8.6 mg/1 1
INACTIVE INGREDIENTS: HYPROMELLOSE, UNSPECIFIED; LACTOSE, UNSPECIFIED FORM; MICROCRYSTALLINE CELLULOSE; CROSPOVIDONE; POVIDONE K30; ISOPROPYL ALCOHOL; MAGNESIUM STEARATE; METHYLENE CHLORIDE

CareMotion Tablets
Natural Vegetable Laxative Ingredient

Active ingredient Purpose
(in each tablet)
Sen nosides 8.6 mg ...................................................Laxative

Purpose

- Laxative

Uses

- relieves occasional constipation (irregularity)
- generally produces a bowel movement in 6-12 hours

Warnings

Do not use

- laxative products for longer than 1 week unless directed by a doctor

Ask a doctor before use if you have

- stomach pain
- nausea
- vomiting
- noticed a sudden change in bowel habits that continues over a period of 2 weeks

Stop use and ask a doctor if

you have rectal bleeding or fail to have a bowel movement after use of a laxative. These may indicate a serious condition.

If pregnant or breast-feeding,

ask a health professional before use.

Keep out of reach of children.

In case of overdose, get medical help or contact a Poison Control Center right away. (1-800-222-1222)

Directions

- take preferably at bedtime or as directed by a doctor

age | starting; dosage | maximum dosage
adults and children 12 years of age and over | 2 tablets once a day | 4 tablets twice a day
children 6 to under 12; years | 1 tablet once a day | 2 tablets twice a day
children 2 to under 6; years | 1 /2 tablet once a day | 1 tablet twice a day
children under 2 years | ask a doctor | ask a doctor

Other information

■ each tablet contains: calcium 5 mg
■ store at 20-25°C (68-77°F); excursions permitted between 15°-30°C (59°-86°F)

Inactive ingredients

crospovidone, dichloromethane, hypromellose, isopropyl alcohol, lactose, magnesium stearate, microcrystalline cellulose, povidone

Questions or Comments? 1-866-561-2888

*This product is not manufactured or distributed by Purdue Products L.P., owner of the registered trademark Senokot

Distributed by:
US Drugs Inc.
11380 7th Street, Rancho Cucamonga, CA 91730, USA
Country of Origin: India